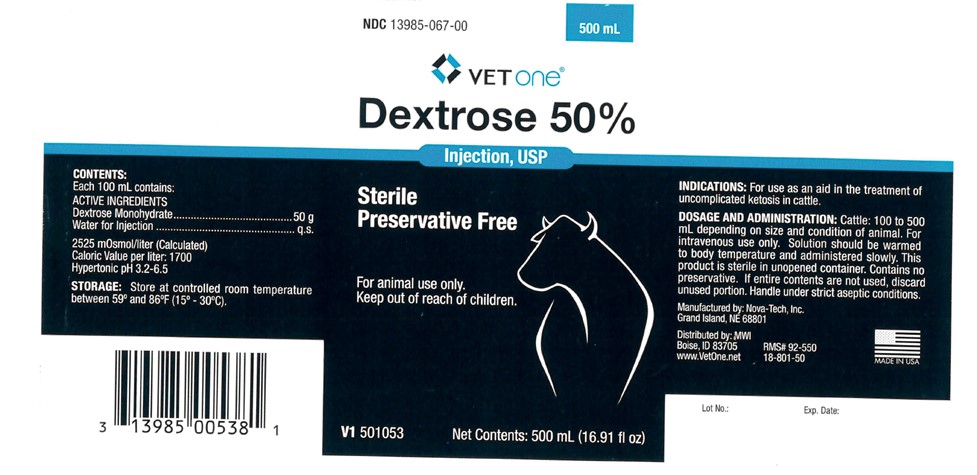 DRUG LABEL: Dextrose
NDC: 13985-067 | Form: INJECTION, SOLUTION
Manufacturer: MWI (VetOne)
Category: animal | Type: OTC ANIMAL DRUG LABEL
Date: 20221216

ACTIVE INGREDIENTS: Dextrose Monohydrate 50 g/100 mL

Dextrose 50%

CONTENTS

Each 100 mL contains:

ACTIVE INGREDIENTS

Dextrose Monohydrate.............................50 g

Water for Injection ...................................q.s.

2525 mOsmol/liter (Calculated)

Caloric Value per liter: 1700

Hypertonic pH 3.2-6.5

STORAGE

Store at controlled room temperature between 59 degrees and 86 degrees F (15 degree - 30 degree C).

VETERINARY INDICATIONS

For animal use only.

Keep out of reach of children.

INDICATIONS

For use as an aid in the treatment of uncomplicated ketosis in cattle.

DOSAGE AND ADMINISTRATION

Cattle: 100 to 500 mL depending on size and condition of animal. For intravenous use only. Solution should be warmed to body temperature and administered slowly. This product is sterile in unopened container. Contains no preservative. If entire contents are not used, discard unused portion. Handle under strict aseptic conditions.

INFORMATION FOR OWNERS/CAREGIVERS

Net contents: 500 mL (16.91 fl oz)

RMS# 92-550

18-801-50